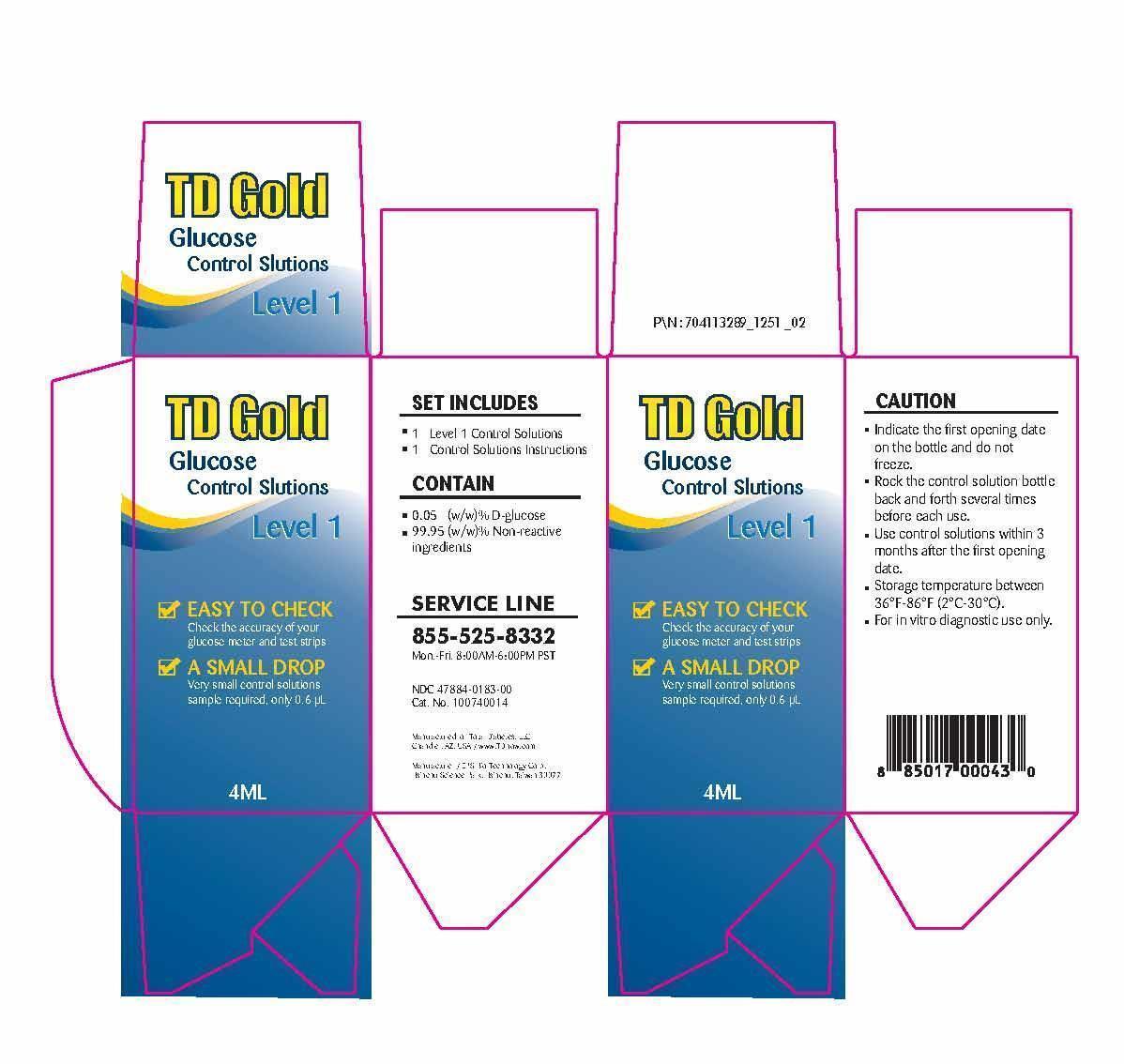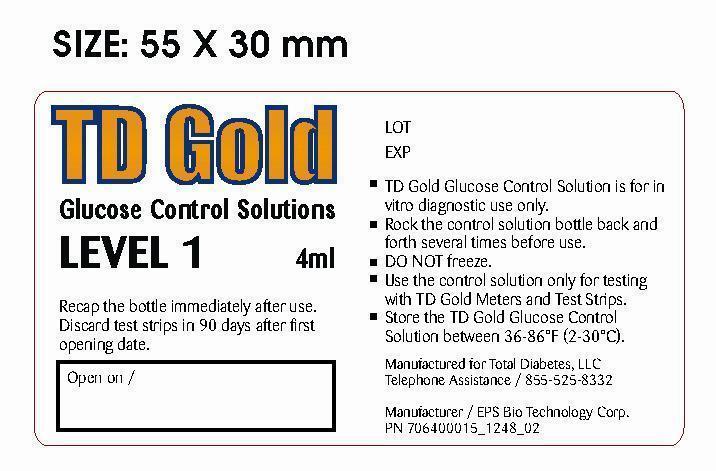 DRUG LABEL: TD Gold Glucose Control Solution Level 1 Set
NDC: 47884-183
Manufacturer: EPS Bio Technology Corp.
Category: other | Type: MEDICAL DEVICE
Date: 20131023

Home Use Medical Device - TD Gold Glucose Control Solution Level 1